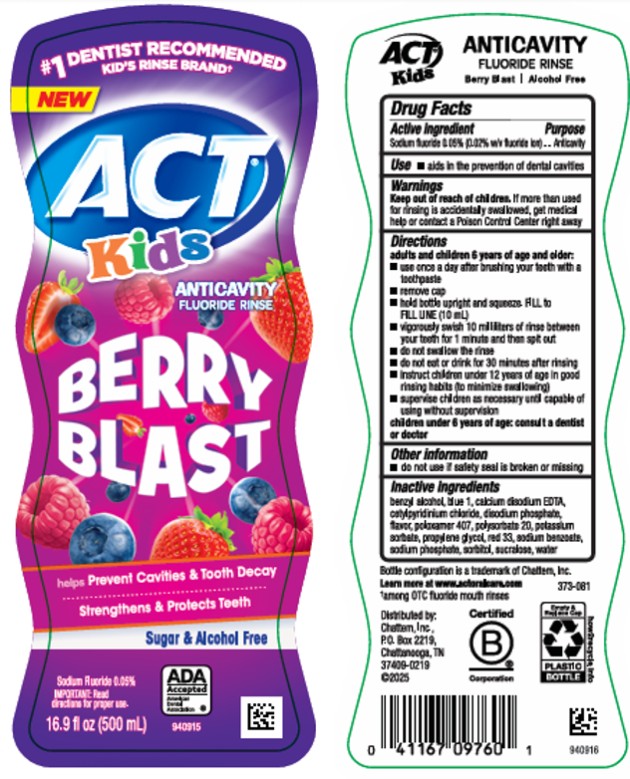 DRUG LABEL: ACT Kids Berry Blast
NDC: 41167-0976 | Form: RINSE
Manufacturer: Chattem, Inc.
Category: otc | Type: HUMAN OTC DRUG LABEL
Date: 20260201

ACTIVE INGREDIENTS: SODIUM FLUORIDE 0.5 mg/1 mL
INACTIVE INGREDIENTS: BENZYL ALCOHOL; BLUE 1; EDETATE CALCIUM DISODIUM ANHYDROUS; CETYLPYRIDINIUM CHLORIDE; SODIUM PHOSPHATE, DIBASIC, ANHYDROUS; POLOXAMER 407; POLYSORBATE 20; POTASSIUM SORBATE; PROPYLENE GLYCOL; RED 33; SODIUM BENZOATE; SODIUM PHOSPHATE; SORBITOL; SUCRALOSE; WATER

ACT Kids Berry Blast Rinse

Drug Facts

Active ingredient

Sodium fluoride 0.05% (0.02% w/v fluoride ion)

Purpose

Anticavity

Use

- aids in the prevention of dental cavities

Warnings

Keep out of reach of children.

If more than used for rinsing is accidentally swallowed, get medical help or contact a Poison Control Center right away.

Directions

adults and children 6 years of age and older:

- use once a day after brushing your teeth with a toothpaste
- remove cap
- hold bottle upright and squeeze. FILL to FILL LINE (10 mL)
- vigorously swish 10 milliliters of rinse between your teeth for 1 minute and then spit out
- do not swallow the rinse
- do not eat or drink for 30 minutes after rinsing
- instruct children under 12 years of age in good rinsing habits (to minimize swallowing)
- supervise children as necessary until capable of using without supervision

children under 6 years of age: consult a dentist or doctor

Other information

■ do not use if safety seal is broken or missing

Inactive ingredients

benzyl alcohol, blue 1, calcium disodium EDTA, cetylpyridinium chloride, disodium phosphate, flavor, poloxamer 407, polysorbate 20, potassium sorbate, propylene glycol, red 33, sodium benzoate, sodium phosphate, sorbitol, sucralose, water

Principal Display Panel

ACT
Kids
ANTICAVITY
FLUORIDE RINSE
BERRY BLAST
16.9 fl oz (500 mL)